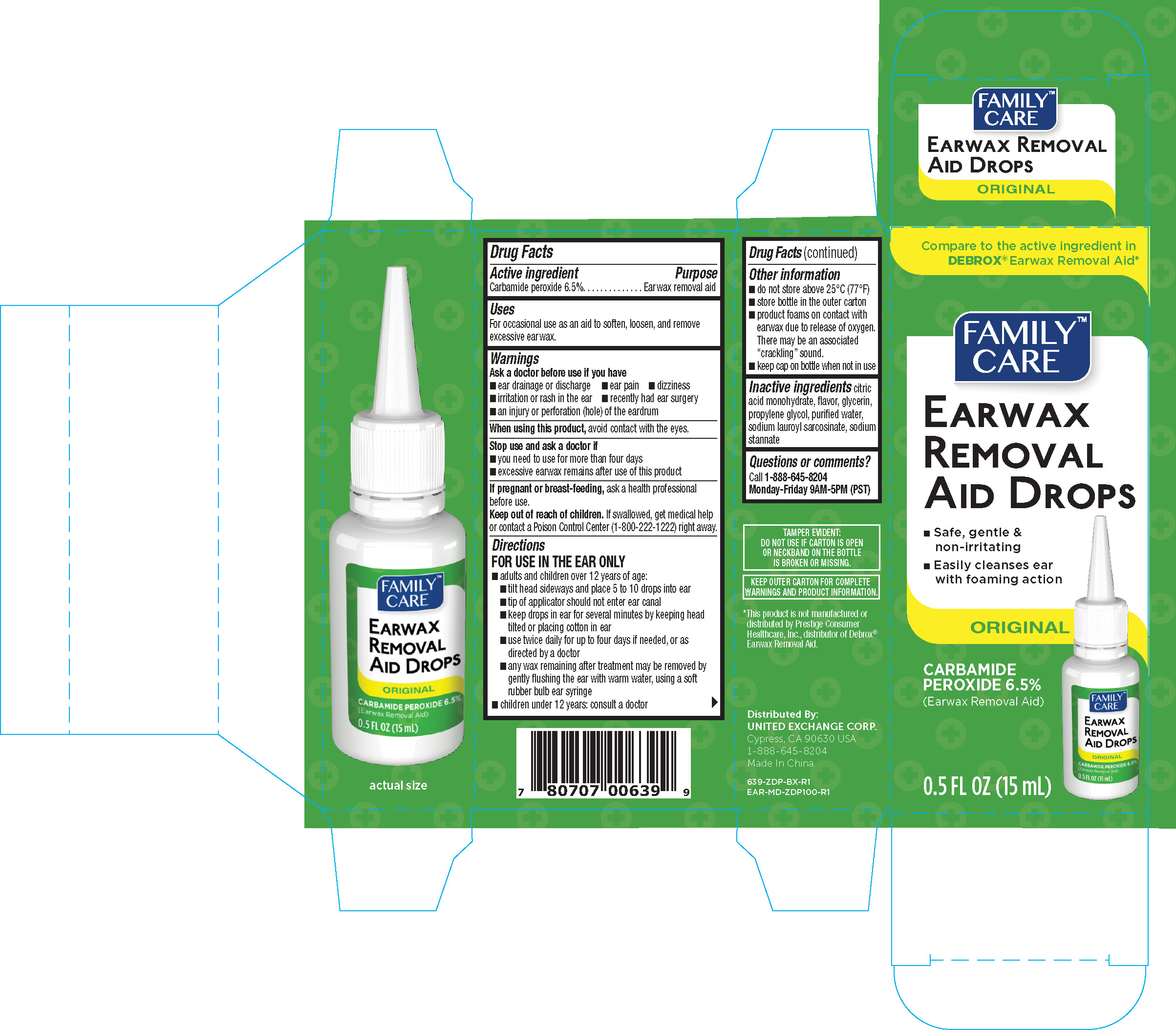 DRUG LABEL: Family Care Earwax Removal
NDC: 65923-639 | Form: LIQUID
Manufacturer: United Exchange Corp.
Category: otc | Type: HUMAN OTC DRUG LABEL
Date: 20251022

ACTIVE INGREDIENTS: CARBAMIDE PEROXIDE 0.065 mg/1 mL
INACTIVE INGREDIENTS: PROPYLENE GLYCOL; CITRIC ACID MONOHYDRATE; SODIUM LAUROYL SARCOSINATE; SODIUM STANNATE; GLYCERIN; WATER

Family Care Earwax Removal Aid Drops 0.5 oz 639 ZDP

Active ingredient Purpose

Carbamide peroxide 6.5%.................................Ear wax removal

Uses

For occasional use as an aid to soften, loosen, and remove excessive ear wax.

Warnings

Ask a doctor before use if you have

- ear drainage or discharge
- ear pain
- dizziness
- irritation or rash in the ear
- recently had ear surgery
- an injury or perforation (hole) of the eardrum

Stop use and ask a doctor if

- you need to use for more than four days
- excessive earwax remains after use of this product

PREGNANCY OR BREAST FEEDING

If pregnant or breast-feeding, ask a health professional before use.

Keep out of reach of children. If swallowed, get medical help or contact a Poison Control Center (1-800-222-1222) right away.

Directions

FOR USE IN THE EAR ONLY

- adults and children over 12 years of age:
- tilt head sideways and place 5 to 10 drops into ear
- tip of applicator should not enter ear canal
- keep drops in ear for several minutes by keeping head tilted or placing cotton in ear
- use twice daily for up to four days if needed, or as directed by a doctor
- any way remaining after treatment may be removed by gently flushing the ear with warm water, using a soft rubber bulb ear syringe
- children under 12 years: consult a doctor

Other information

- do not store above 25°C (77°F)
- store bottle in the outer carton
- product foams on contact with earwax due to release of oxygen. There may be associated "crackling" sound
- keep cap on bottle when not in use

Inactive ingredients

citric acid monohydrate, flavor, glycerin, propylene glycol, purified water, sodium lauroyl sarcosinate, sodium stannate

DOSAGE AND ADMINISTRATION

Distributed by:

United Exchange Corp.

Cypress, CA 90630

Made in China